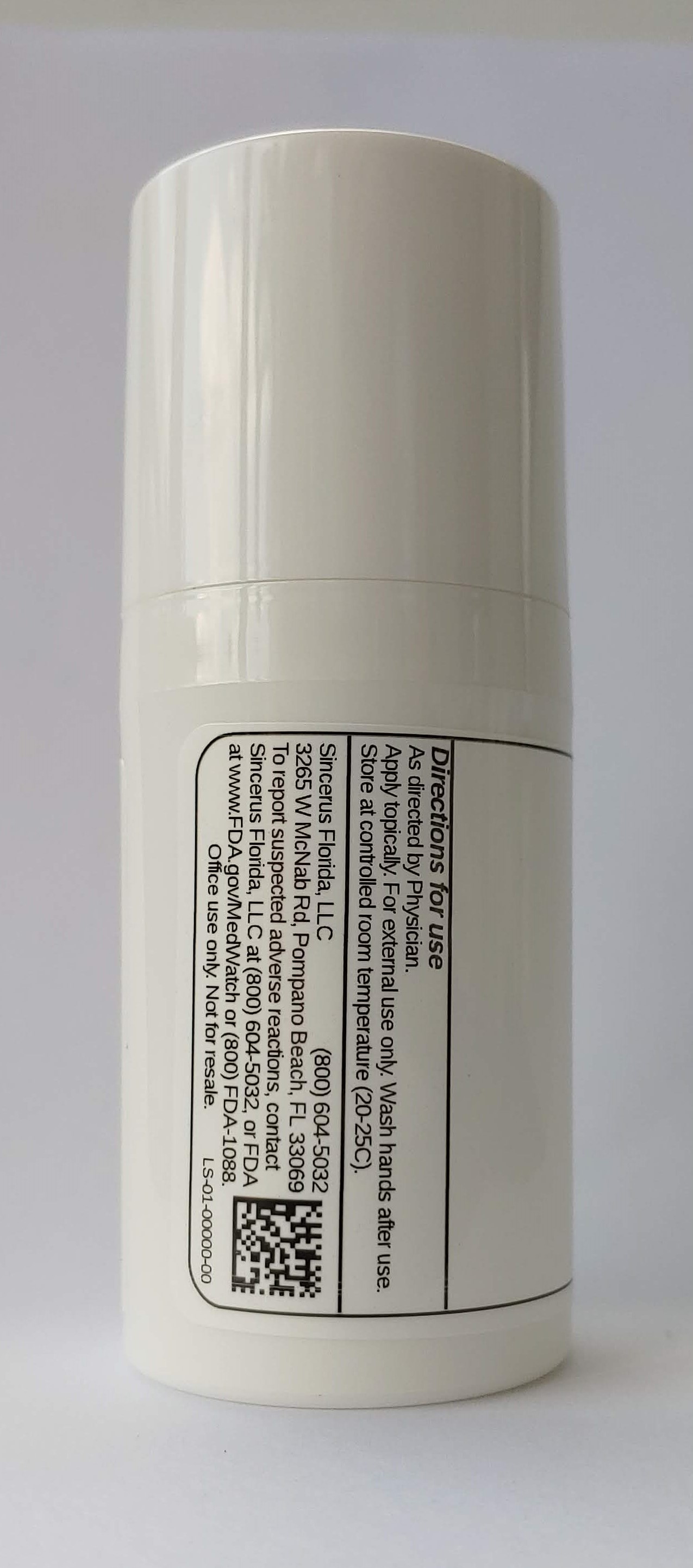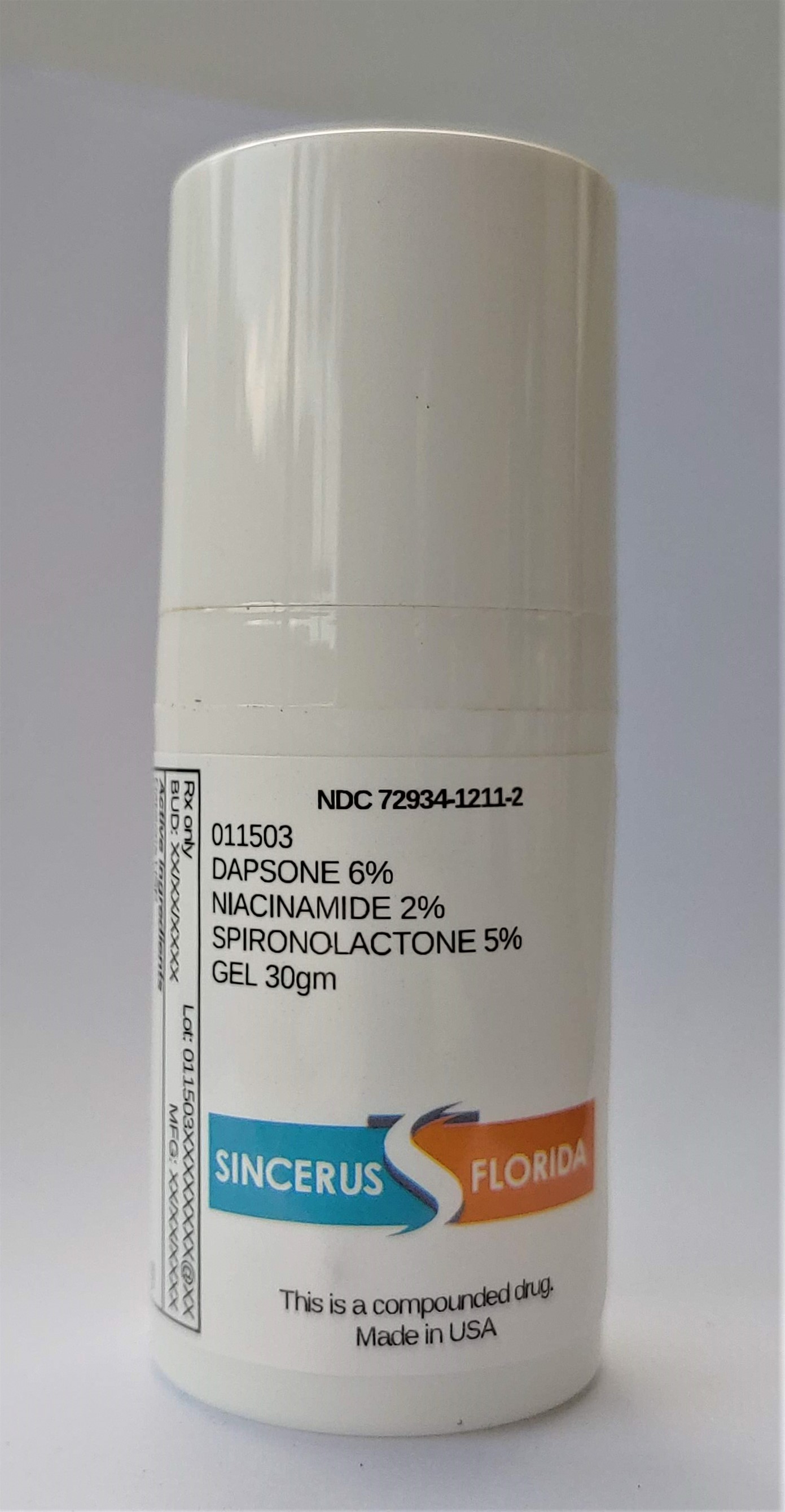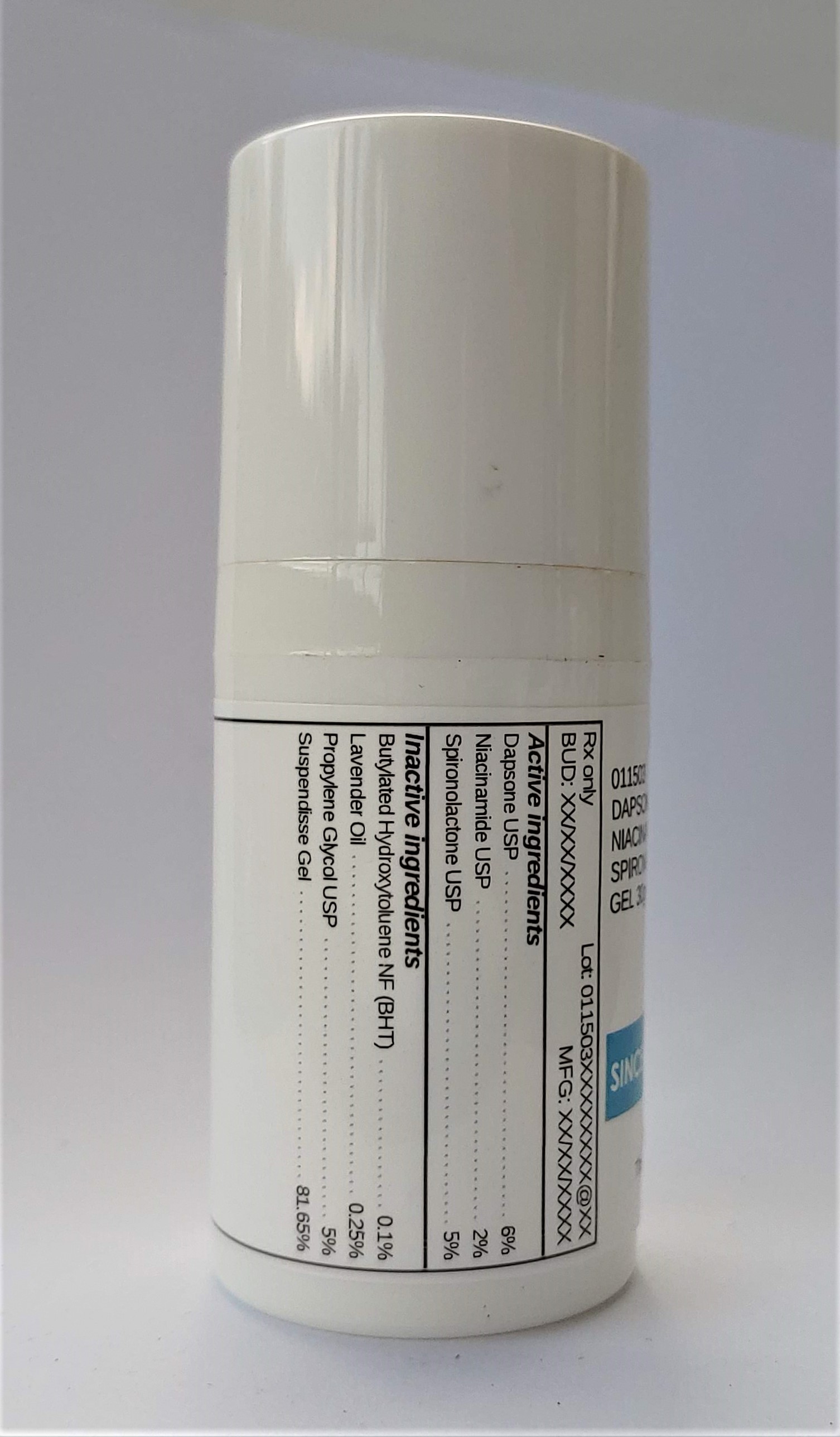 DRUG LABEL: 011503 DAPSONE 6% / NIACINAMIDE 2% / SPIRONOLACTONE 5%
NDC: 72934-1211 | Form: GEL
Manufacturer: Sincerus Florida, LLC
Category: prescription | Type: HUMAN PRESCRIPTION DRUG LABEL
Date: 20200702

ACTIVE INGREDIENTS: NIACINAMIDE 2 g/100 g; SPIRONOLACTONE 5 g/100 g; DAPSONE 6 g/100 g

011503 DAPSONE 6% / NIACINAMIDE 2% / SPIRONOLACTONE 5%